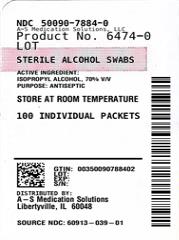 DRUG LABEL: Alcohol
NDC: 50090-7884 | Form: SWAB
Manufacturer: A-S Medication Solutions
Category: otc | Type: HUMAN OTC DRUG LABEL
Date: 20260208

ACTIVE INGREDIENTS: ISOPROPYL ALCOHOL 70 mL/100 mL
INACTIVE INGREDIENTS: AQUA

Ultimed Alcohol Swabs 100ct, 200ct

Active Ingredients

Isopropyl alcohol 70% v/v

Purpose

Antiseptic

Use

For preparation of the skin prior to injection; to decrease germs in minor cuts and scrapes.

Warnings

For external use only. Flammable; keep away from fire and flame.

Keep out of reach of children

If swallowed, get medical help or contact a Poison Control Center immediately.

Caution

Do not apply to irritated skin.

Do not use

in the eyes, or on mucous membranes. In case of deep or puncture wounds, consult a doctor.

Directions

Wipe injection site vigorously.

Other Information

Store at room temperature

Inactive Ingredients

Water